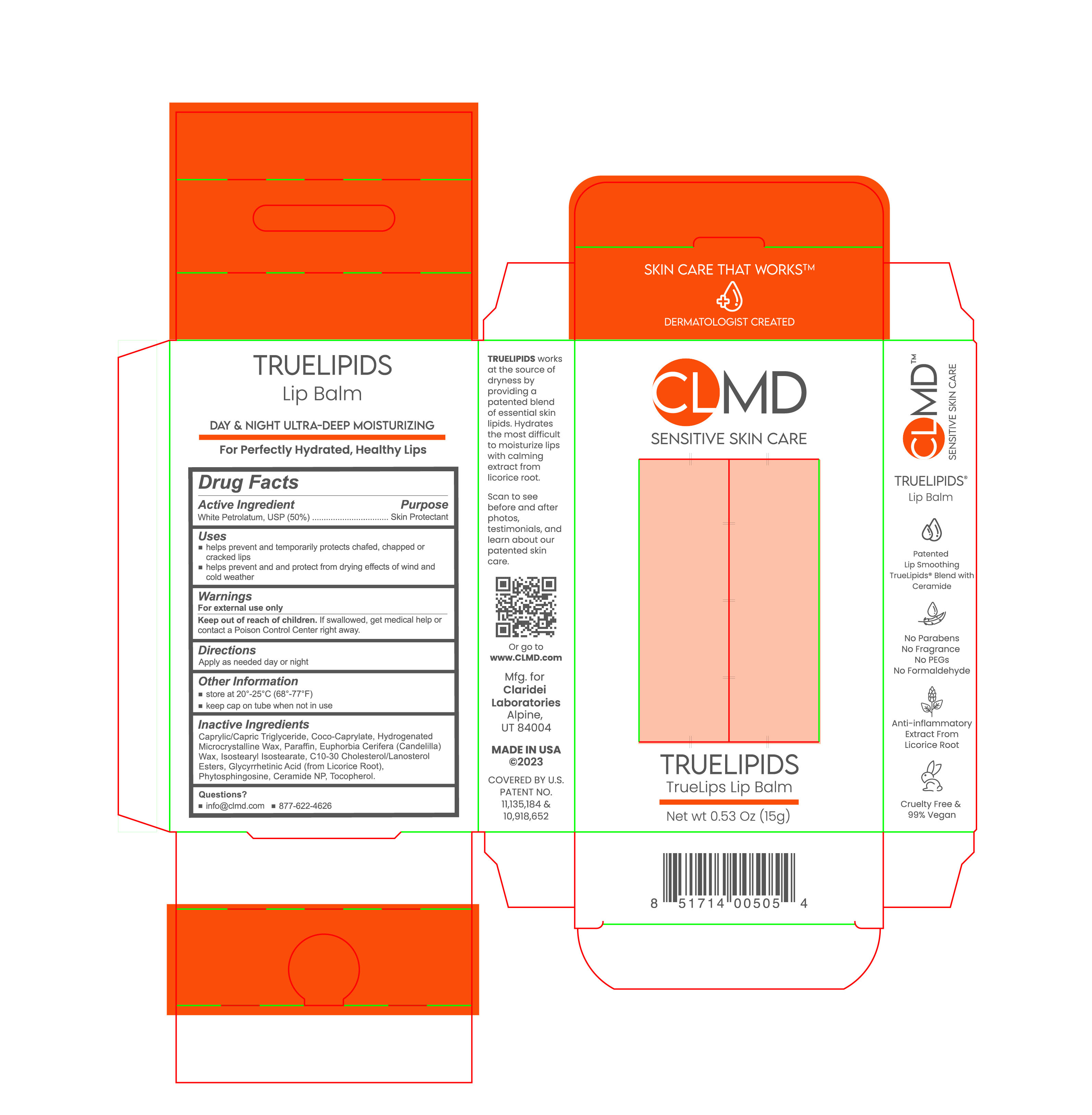 DRUG LABEL: Truelipids TrueLips Lip Balm
NDC: 61387-255 | Form: SOLUTION
Manufacturer: Claridei Laboratories, Inc.
Category: otc | Type: HUMAN OTC DRUG LABEL
Date: 20251215

ACTIVE INGREDIENTS: PETROLATUM 50 g/100 g
INACTIVE INGREDIENTS: C10-30 CHOLESTEROL/LANOSTEROL ESTERS; MEDIUM-CHAIN TRIGLYCERIDES; CERAMIDE NP; COCO-CAPRYLATE; CANDELILLA WAX; ENOXOLONE; ISOSTEARYL ISOSTEARATE; MICROCRYSTALLINE WAX; PARAFFIN; PHYTOSPHINGOSINE; TOCOPHEROL

Truelipids TrueLips Lip Balm

Active Ingredient purpose

White Petrolatum 50% Skin Protectant (ointment)

Uses

- helps prevent and temporarily protects chafed, chapped,or cracked lips
- helps prevent and protect from the drying effects of wind and cold weather

Keep out of reach of children. If swallowed, get medical help or contact a Poison Control Center right away.

Keep out of reach of children. If swallowed, get medical help or contact a Poison Control Center right away.

Warnings

For external use only

Directions

- apply as needed day or night

Inactive Ingredients:

Carpylic/Capric Triglyceride, Coco-Caprylate, Hydrogenated Microcrystalline Wax, Paraffin, Euphorbia Cerifera (Candelilla) Wax, Isostearyl Isostearate, C10-30 Cholesterol/Lanosterol Esters, Glycyrrhetinic Acid(from Licorice Root), Phytosphingosine, Ceramide NP, Tocopherol

PACKAGE LABEL

CL MD

Sensitive Skin Care

TRUELIPIDS

Truelipids Lip Balm

Net Wt 0.53 Oz (15g)